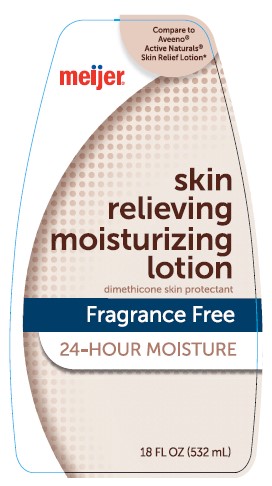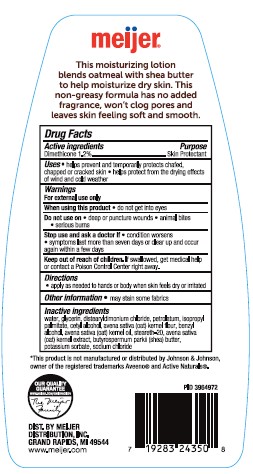 DRUG LABEL: Meijer
NDC: 41250-985 | Form: LOTION
Manufacturer: MEIJER DISTRIBUTION, INC
Category: otc | Type: HUMAN OTC DRUG LABEL
Date: 20241016

ACTIVE INGREDIENTS: DIMETHICONE 12 mg/1 mL
INACTIVE INGREDIENTS: WATER; GLYCERIN; ISOPROPYL PALMITATE; SHEA BUTTER; DISTEARYLDIMONIUM CHLORIDE; OATMEAL; POTASSIUM SORBATE; SODIUM CHLORIDE; PETROLATUM; CETYL ALCOHOL; OAT KERNEL OIL; STEARETH-20; OAT; BENZYL ALCOHOL

Meijer Skin Relieving Moisturizing Lotion

Active ingredients

Dimethicone 1.2%

Purpose

Skin Protectant

Uses

- helps prevent and temporarily protects chafed, chapped or cracked skin
- helps protect from the drying effects of wind and cold weather

Warnings

For external use only

When using this product • do not get into eyes

Do not use on

- deep or puncture wounds
- animal bites
- serious burns

Stop use and ask a doctor if

- condition worsens
- symptoms last more than seven days or clear up and occur again within a few days

Keep out of reach of children. If swallowed, get medical help or contact a Poison Control Center right away.

Directions

- apply as needed to hands or body when skin feels dry or irritated

Other Information • may stain some fabrics

Inactive ingredients

water, glycerin, distearyldimonium chloride, petrolatum, isopropyl palmitate, cetyl alcohol, avena sativa (oat) kernel flour, benzyl alcohol, avena sativa (oat) kernel oil, steareth-20, avena sativa (oat) kernel extract, butyrospermum parkii (shea) butter, potassium sorbate, sodium chloride

PACKAGE LABEL

Meijer Skin Relieving Moisturizing Lotion

18 fl oz (532mL)

NDC 41250-990-43